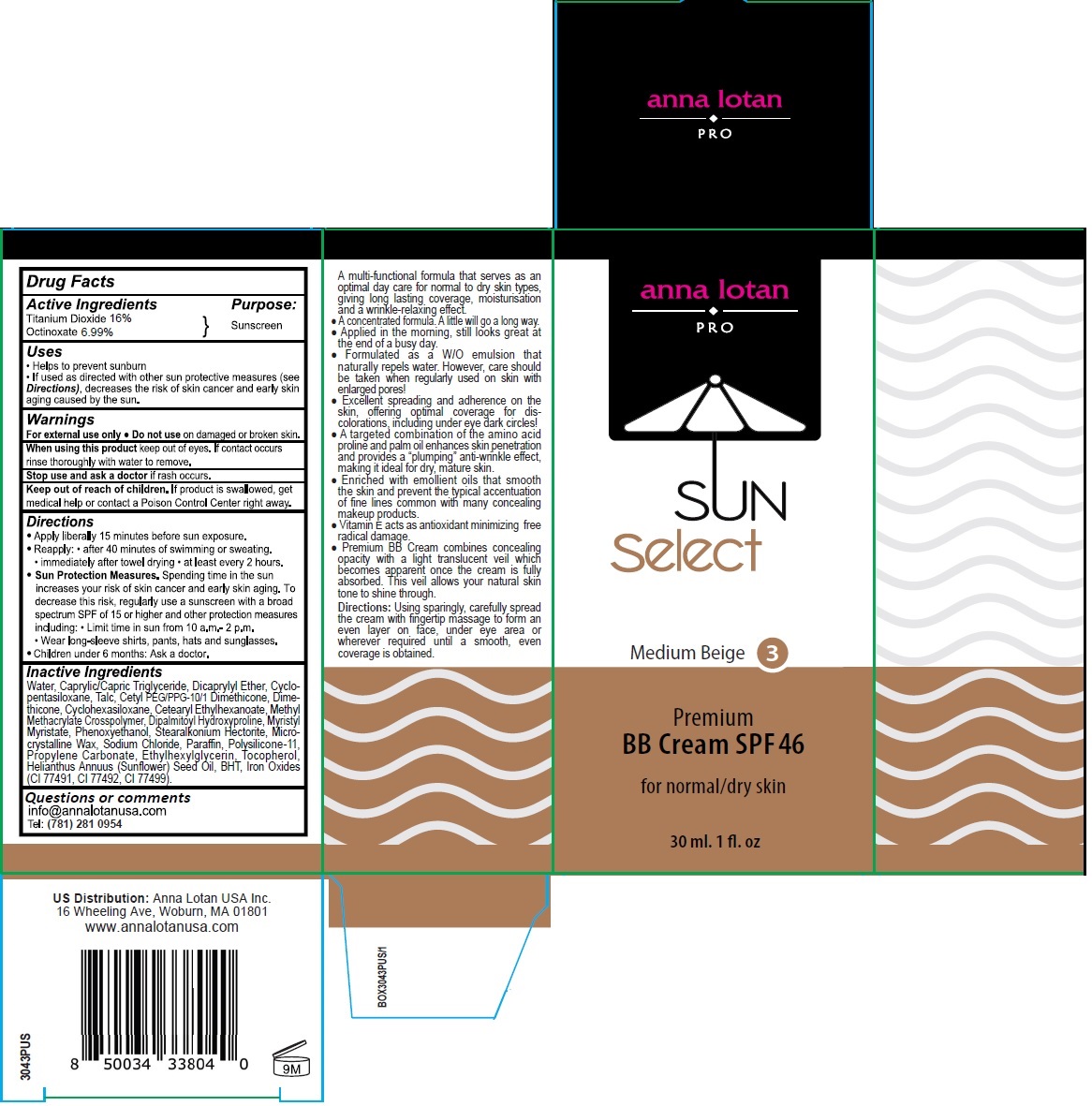 DRUG LABEL: anna lotan Premium BB Cream SPF46 Medium Beige
NDC: 76446-043 | Form: CREAM
Manufacturer: Anna Lotan Ltd
Category: otc | Type: HUMAN OTC DRUG LABEL
Date: 20250924

ACTIVE INGREDIENTS: TITANIUM DIOXIDE 16 g/100 mL; OCTINOXATE 6.99 g/100 mL
INACTIVE INGREDIENTS: WATER; MEDIUM-CHAIN TRIGLYCERIDES; DICAPRYLYL ETHER; CYCLOMETHICONE 5; TALC; CETYL PEG/PPG-10/1 DIMETHICONE (HLB 5); DIMETHICONE, UNSPECIFIED; CYCLOMETHICONE 6; CETEARYL ETHYLHEXANOATE; METHYL METHACRYLATE/GLYCOL DIMETHACRYLATE CROSSPOLYMER; DIPALMITOYL HYDROXYPROLINE; MYRISTYL MYRISTATE; PHENOXYETHANOL; STEARALKONIUM HECTORITE; MICROCRYSTALLINE WAX; SODIUM CHLORIDE; PARAFFIN; DIMETHICONE/VINYL DIMETHICONE CROSSPOLYMER (SOFT PARTICLE); PROPYLENE CARBONATE; ETHYLHEXYLGLYCERIN; TOCOPHEROL; SUNFLOWER OIL; BUTYLATED HYDROXYTOLUENE; FERRIC OXIDE RED; FERRIC OXIDE YELLOW; FERROSOFERRIC OXIDE

anna lotan Premium BB Cream SPF46 Medium Beige

Active Ingredients

Titanium Dioxide 16%
Octinoxate 6.99%

Purpose:

Sunscreen

Uses

• Helps to prevent sunburn
• If used as directed with other sun protective measures (see Directions), decreases the risk of skin cancer and early skin aging caused by the sun.

Warnings

For external use only • Do not use on damaged or broken skin.

When using this product keep out of eyes. If contact occurs rinse thoroughly with water to remove.

Stop use and ask a doctor if rash occurs.

Keep out of reach of children. If product is swallowed, get medical help or contact a Poison Control Center right away.

Directions

• Apply liberally 15 minutes before sun exposure.
• Reapply: • after 40 minutes of swimming or sweating. • immediately after towel drying • at least every 2 hours.
• Sun Protection Measures. Spending time in the sun increases your risk of skin cancer and early skin aging. To decrease this risk, regularly use a sunscreen with a broad spectrum SPF of 15 or higher and other protection measures including: • Limit time in sun from 10 a.m.- 2 p.m. • Wear long-sleeve shirts, pants, hats and sunglasses.
• Children under 6 months: Ask a doctor.

Inactive Ingredients

Water, Caprylic/Capric Triglyceride, Dicaprylyl Ether, Cyclopentasiloxane, Talc, Cetyl PEG/PPG-10/1 Dimethicone, Dimethicone, Cyclohexasiloxane, Cetearyl Ethylhexanoate, Methyl Methacrylate Crosspolymer, Dipalmitoyl Hydroxyproline, Myristyl Myristate, Phenoxyethanol, Stearalkonium Hectorite, Microcrystalline Wax, Sodium Chloride, Paraffin, Polysilicone-11, Propylene Carbonate, Ethylhexylglycerin, Tocopherol, Helianthus Annuus (Sunflower) Seed Oil, BHT, Iron Oxides (CI 77491, CI 77492, CI 77499).

Questions or comments

info@annalotanusa.com
Tel: (781) 281 0954

PRO

SUN Select

Medium Beige 3

for normal/dry skin

A multi-functional formula that serves as an optimal day care for normal to dry skin types, giving long lasting coverage, moisturisation and a wrinkle-relaxing effect.
• A concentrated formula. A little will go a long way.
• Applied in the morning, still looks great at the end of a busy day.
• Formulated as a W/O emulsion that naturally repels water. However, care should be taken when regularly used on skin with enlarged pores!
• Excellent spreading and adherence on the skin, offering optimal coverage for discolorations, including under eye dark circles!
• A targeted combination of the amino acid proline and palm oil enhances skin penetration and provides a “plumping” anti-wrinkle effect, making it ideal for dry, mature skin.
• Enriched with emollient oils that smooth the skin and prevent the typical accentuation of fine lines common with many concealing makeup products.
• Vitamin E acts as antioxidant minimizing free radical damage.
• Premium BB Cream combines concealing opacity with a light translucent veil which becomes apparent once the cream is fully absorbed. This veil allows your natural skin tone to shine through.

Directions: Using sparingly, carefully spread the cream with fingertip massage to form an even layer on face, under eye area or wherever required until a smooth, even coverage is obtained.

US Distribution: Anna Lotan USA Inc.
16 Wheeling Ave, Woburn, MA 01801
www.annalotanusa.com